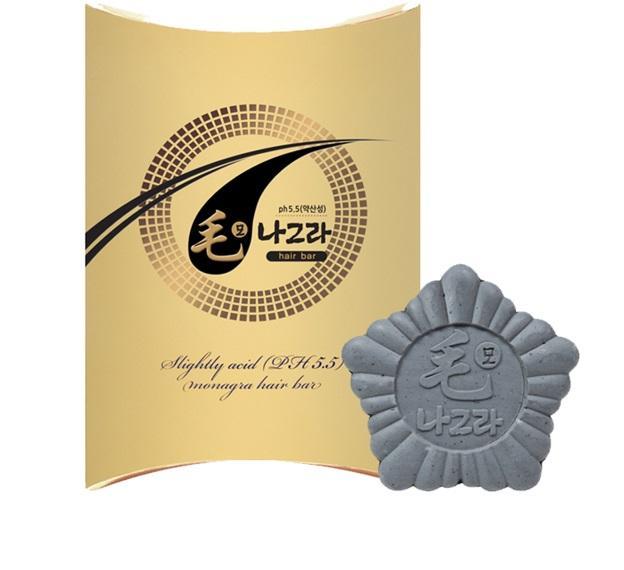 DRUG LABEL: Monagra
NDC: 69196-2002 | Form: SOAP
Manufacturer: Sungwon Cosmetics
Category: otc | Type: HUMAN OTC DRUG LABEL
Date: 20230131

ACTIVE INGREDIENTS: GLYCERIN 1 g/100 g
INACTIVE INGREDIENTS: ORANGE OIL; ALOE; ASCORBIC ACID

Monagra 69196-2002-1

ACTIVE INGREDIENT

glycerin

INACTIVE INGREDIENT

vitamin c, jojoba oil, aloe vera, black bean, ginseng extract, ginseng flower powder, orange oil, jade powder etc

PURPOSE

prevent hair loss
strengthen remaining hair
protect scalp

keep out of reach of the children

INDICATIONS AND USAGE

Foaming and applying to scalp and massage with slightly strength
Wait for about 10 seconds and massage again
Wash away the foam with clean water.

WARNINGS

do not swallow
do not use if you have skin wounds
do not use if you have allergies

DOSAGE AND ADMINISTRATION

for topical use only